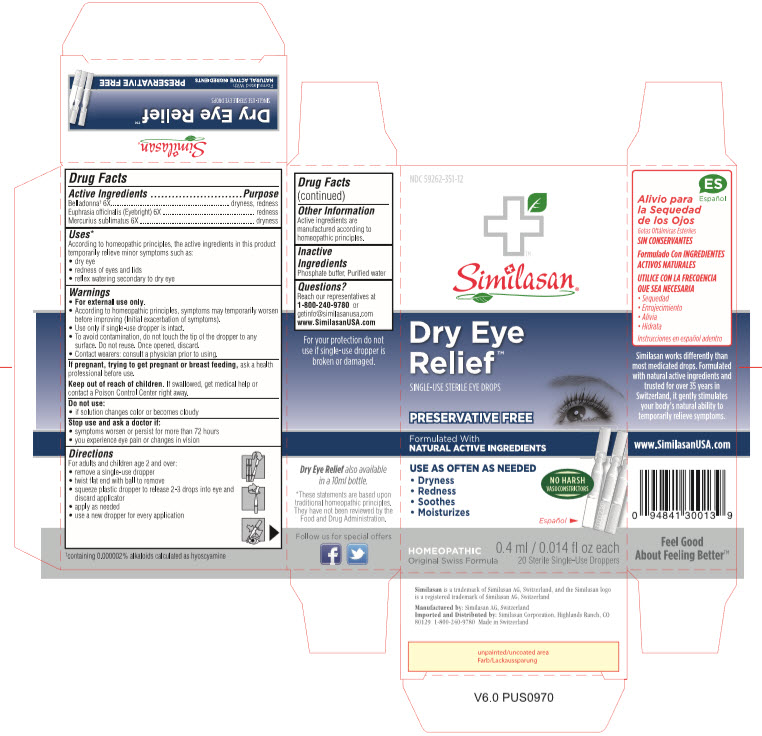 DRUG LABEL: Dry Eye Relief
NDC: 59262-351 | Form: SOLUTION/ DROPS
Manufacturer: Similasan Corporation
Category: homeopathic | Type: HUMAN OTC DRUG LABEL
Date: 20190320

ACTIVE INGREDIENTS: ATROPA BELLADONNA 6 [hp_X]/0.4 mL; EUPHRASIA STRICTA 6 [hp_X]/0.4 mL; MERCURIC CHLORIDE 6 [hp_X]/0.4 mL
INACTIVE INGREDIENTS: WATER; SODIUM PHOSPHATE, MONOBASIC, DIHYDRATE; SODIUM PHOSPHATE, DIBASIC, ANHYDROUS

Similasan Dry Eye Relief Preservative Free

Active Ingredient

Belladonna* 6X

ACTIVE INGREDIENT

Enter section text here

*containing 0.000002% alkaloids calculated as hyoscyamine.

Purpose

dryness, redness

Active Ingredient

Euphrasia 6X

Purpose

redness, inflammation

Active Ingredient

Mercurius sublimatus 6X

Purpose

dryness

Uses

According to homeopathic principles, the active ingredients in this medication temporarily minor symptoms such as:

- dry eye
- redness of eyes and lids
- reflex watering secondary to dry eye
- sensation of grittiness
- sensitivity to light

Warnings

- For external use only.
- Initial exacerbation of symptoms may occur.
- Use only if single-use dropper is intact.
- To avoid contamination, do not touch the tip of the dropper to any surface. Do not reuse. Once opened, discard.
- Contact wearers: consult a physician prior to using.

Do not use:

- if the solution changes color or becomes cloudy

Stop use and ask a doctor if:

- symptoms worsen or persist for more than 72 hours.
- changes in vision occur.
- you experience eye pain.

If pregnant or breast feeding,

ask a health professional before use.

Keep out of reach of children.

If swallowed, get medical help or contact a Poison Control Center right away.

Directions

For adults and children age 2 and over:

- remove a single use dropper
- twist flat end with ball to remove
- squeeze plastic tip to release 2-3 drops into eye and discard applicator
- apply as needed throughout the day or night
- use a dropper for every application

Other information

Active ingredients are manufactured according to homeopathic principles and are therefore non-toxic and have no known side effects.

Inactive Ingredients

Phosphate buffer, Purified water

Questions?

Reach our representatives, M-F, 8am-5pm (MT), or our 24 hour recorded product information at 1-800-240-9780. Visit us: www.SimilasanUSA.com

Principal Display Panel

NDC 59262-351-12
Similasan
Dry Eye
Relief
SINGLE-USE STERILE EYE DROPS
Preservative Free
0.4 ml/ 0.014 fl oz each
20 Sterile Single-Use Droppers